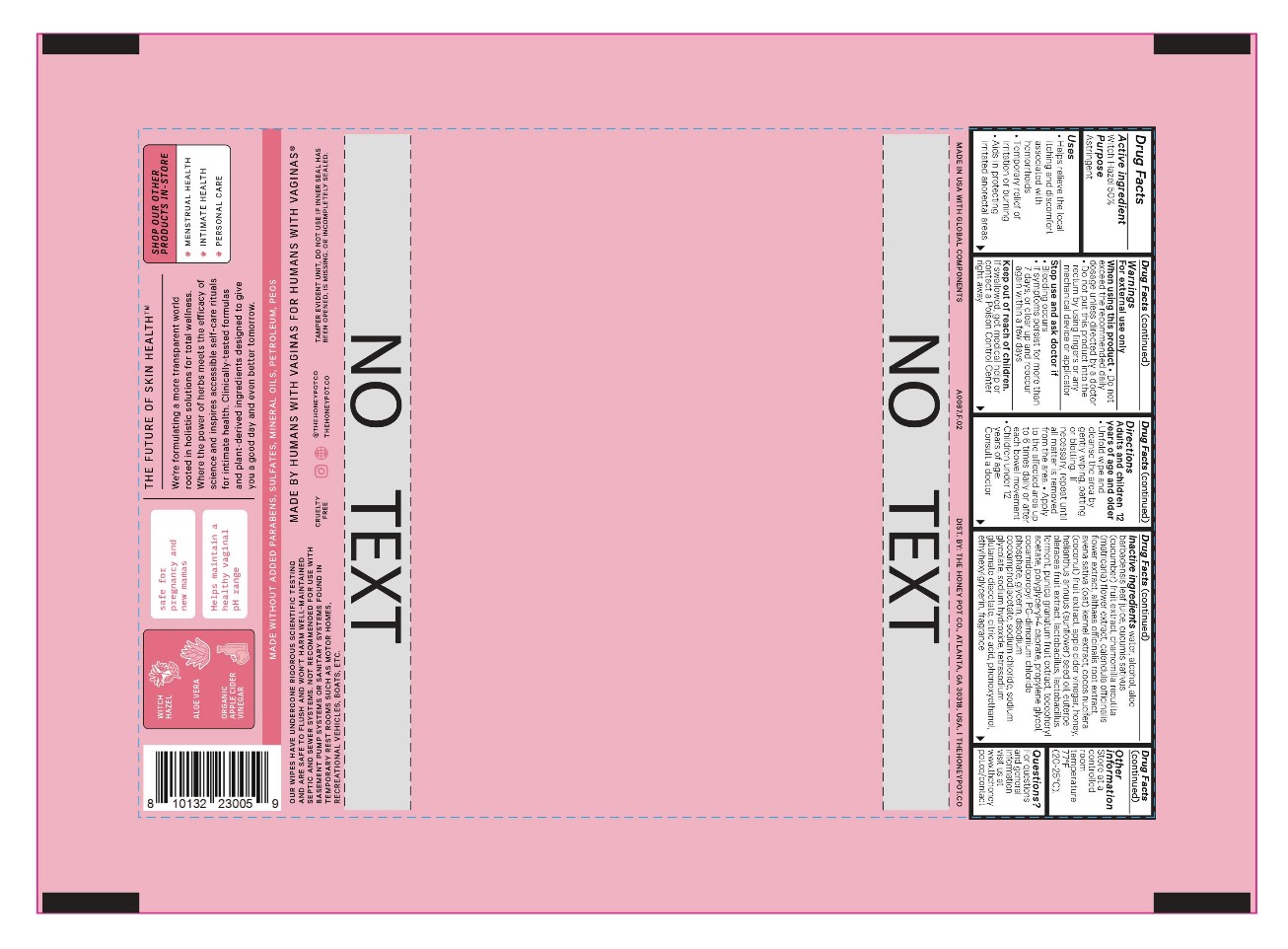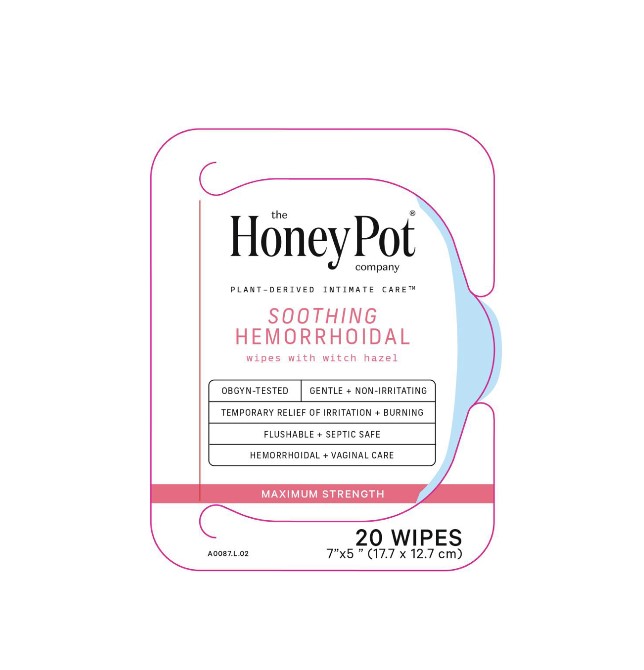 DRUG LABEL: Soothing Hemorrhoidal Wipes 50 Witch Hazel
NDC: 82637-0059 | Form: CLOTH
Manufacturer: The Honey Pot Company LLC
Category: otc | Type: HUMAN OTC DRUG LABEL
Date: 20240801

ACTIVE INGREDIENTS: WITCH HAZEL 500 mg/1 mL
INACTIVE INGREDIENTS: SODIUM HYDROXIDE; LIMOSILACTOBACILLUS FERMENTUM; ALOE VERA LEAF; OAT; CALENDULA OFFICINALIS FLOWER; CHAMOMILE; CITRIC ACID MONOHYDRATE; COCAMIDOPROPYL PROPYLENE GLYCOL-DIMONIUM CHLORIDE PHOSPHATE; COCONUT; CUCUMBER; DISODIUM COCOAMPHODIACETATE; ETHYLHEXYLGLYCERIN; ACAI; GLYCERIN; SUNFLOWER OIL; HONEY; PHENOXYETHANOL; POLYGLYCERYL-4 CAPRATE; POMEGRANATE; SODIUM CHLORIDE; TETRASODIUM GLUTAMATE DIACETATE; .ALPHA.-TOCOPHEROL ACETATE; WATER; APPLE CIDER VINEGAR; ALTHAEA OFFICINALIS ROOT; PROPYLENE GLYCOL; BIFIDOBACTERIUM ANIMALIS LACTIS; ALCOHOL; SODIUM GLYCOLATE

Soothing Hemorrhoidal Wipes with Witch Hazel

Active Ingredient:

Witch Hazel 50%

Purpose:

Astringent

Uses:

- Helps relieve the local itching and discomfort associated with hemorrhoids
- Temporary relief of irritation or burning
- Aids in protecting irritated anorectal areas

Warnings:

For external use only

When using this product:

- Do not exceed the recommended daily dosage unless directed by a doctor
- Do not put this product into the rectum by using fingers or any mechanical device or applicator

Stop use and ask doctor if:

- Bleeding occurs
- If symptoms persist for more than 7 days, or clear up and reoccur again within a few days.

Keep out of reach of of reach of children.

If swallowed, get medical help or contact a Poison Control Center right away.

Directions:

Adults and children 12 years of age and older:

- Unfold wipe and cleanse the area by gently wiping, patting or blotting. If necessary, repeat until all matter is removed from the area
- Apply to the affected area up to 6 times daily or after each bowel movement

Children under 12 years of age: Consult a doctor

Inactive Ingredients:

water, alcohol, aloe barbadensis leaf juice, cucumis sativus (cucumber) fruit extract, chamomilla recutita (matricaria) flower extract, calendula officinalis flower extract, althaea officinalis root extract, avena sativa (oat) kernel extract, cocos nucifera (coconut) fruit extract, apple cider vinegar, honey, helianthus annuus (sunflower) seed oil, euterpe oleracea fruit extract, lactobacillus, lactobacillus ferment, punica granatum fruit extract, tocopheryl acetate, polyglyceryl-4 caprate, propylene glycol, cocamidopropyl PG-dimonium chloride phosphate, glycerin, disodium cocoamphodiacetate, sodium chloride, sodium glycolate, sodium hydroxide, tetrasodium glutamate diacetate, citric acid, phenoxyethanol, ethylhexylglycerin, fragrance

Other Information:

Store at a controlled room temperature 77°F (20-25°C).

Questions:

For questions and general information visit us at www.thehoneypot.co/contact

Prinicpal Display Panel:

THE HONEY POT COMPANY

PLANT-DERIVED INTIMATE CARE

SOOTHING

HEMORRHOIDAL

wipes with witch hazel

OBGYN – TESTED

GENTLE + NON-IRRITATING

TEMPORARY RELIEF OF IRRITATION + BURNING

FLUSHABLE + SEPTIC SAFE

HEMORRHOIDAL + VAGINAL CARE

MAXIMUM STRENGTH

20 WIPES

7 x 5 in. (17.7 x 12.7 cm)